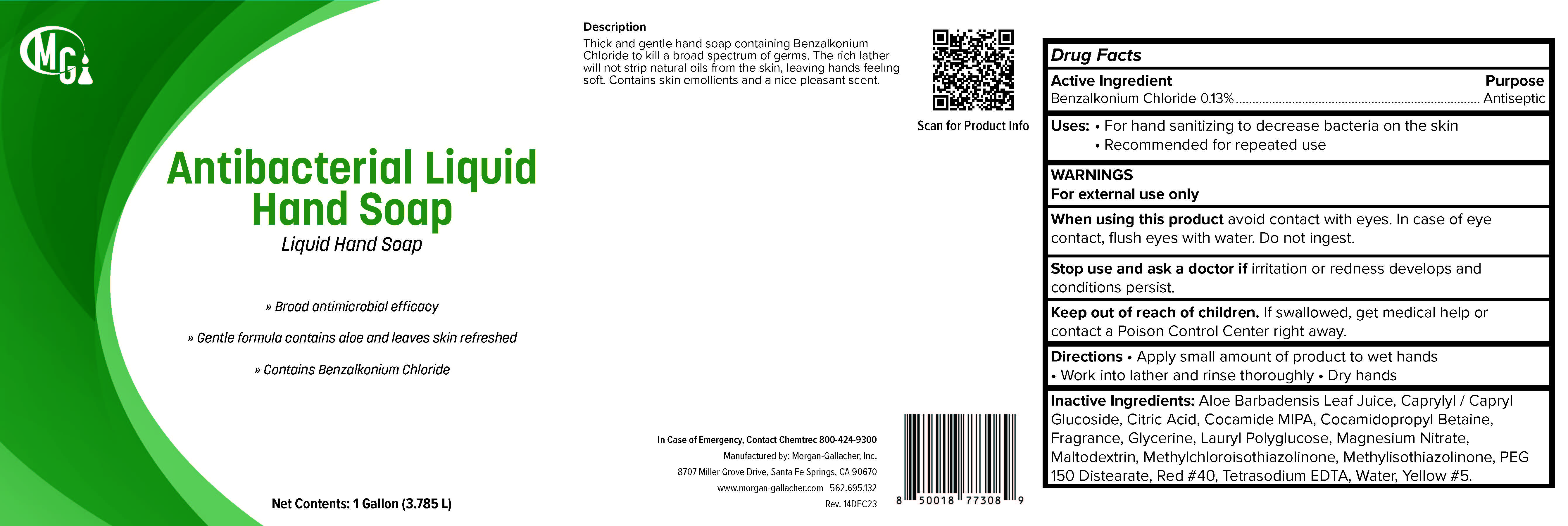 DRUG LABEL: Antibacterial Liquid Hand
NDC: 50241-317 | Form: LIQUID
Manufacturer: Morgan Gallacher Inc. DBA Custom Chemical Formulators Inc.
Category: otc | Type: HUMAN OTC DRUG LABEL
Date: 20251223

ACTIVE INGREDIENTS: BENZALKONIUM CHLORIDE 13 kg/100 kg
INACTIVE INGREDIENTS: ALOE VERA LEAF; CAPRYLYL/CAPRYL OLIGOGLUCOSIDE; ANHYDROUS CITRIC ACID; COCO MONOISOPROPANOLAMIDE; COCAMIDOPROPYL BETAINE; GLYCERIN; LAURYL GLUCOSIDE; MAGNESIUM NITRATE; MALTODEXTRIN; METHYLCHLOROISOTHIAZOLINONE; METHYLISOTHIAZOLINONE; PEG-150 DISTEARATE; FD&C RED NO. 40; EDETATE SODIUM; WATER; FD&C YELLOW NO. 5

Antibacterial Liquid Hand Soap

ACTIVE INGREDIENT

Benzalkonium Chloride........0.13%

Purpose

Antiseptic

Uses

For hand washing to decrease bacteria on the skin.

Warnings

For external use only.

When Using this Product

Avoid contact with the eyes.

In case of eye contact, flush eyes with water.

Stop use and ask a doctor if irritation or redness develops

or if condition persist for more than 72 hours.

Keep out of reach of children.

If swallowed, get medical help

or contact Posion Control Center right away.

Directions

-Pump into hands, wet as needed.

-Lather skin Vigorously for at least 15 seconds.

-Wash skin, rinse thoroughly and dry.

Inactive Ingredients

Aloe Barbadensis Leaf Juice, Caprylyl/Capryl Glucoside, Citric Acid, Cocamide MIPA, Cocamidopropyl Betaine, Fragrance, Glycerin, Lauryl Polyglucose, Magnesium Nitrate, Maltodextrin, Methylchloroisothiazolinone, Methylisothiazolinone, PEG 150 Distearate, FD&C Red #40, Tetrasodium EDTA, Water, FD&C Yellow #5